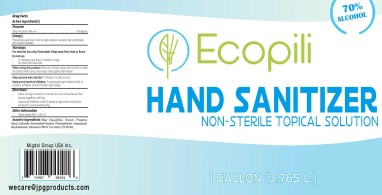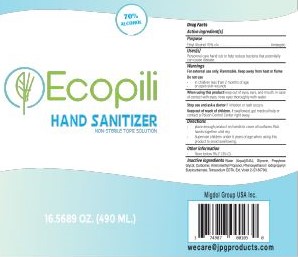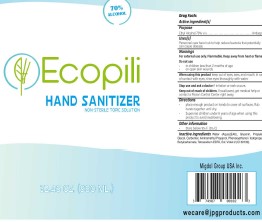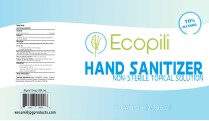 DRUG LABEL: Hand Sanitizer
NDC: 75470-800 | Form: GEL
Manufacturer: Tecnoglobal Ph7, S.a. De C.v.
Category: otc | Type: HUMAN OTC DRUG LABEL
Date: 20200903

ACTIVE INGREDIENTS: ALCOHOL 70 mL/100 mL
INACTIVE INGREDIENTS: PROPYLENE GLYCOL; AMINOMETHYLPROPANOL; CARBOMER 940; GLYCERIN; WATER; PHENOXYETHANOL; EXT. D&C VIOLET NO. 2; IODOPROPYNYL BUTYLCARBAMATE; EDETATE SODIUM

Ecopili 75470-800

Active Ingredient(s)

Alcohol 70% v/v. Purpose: Antiseptic

Purpose

Antiseptic

Use

Personal care hand rub to help reduce bacteria that potentially can cause disease.

Warnings

For external use only. Flammable. Keep away from heat or flame

Do not use

- in children less than 2 months of age
- on open skin wounds

When using this product keep out of eyes, ears, and mouth. In case of contact with eyes, rinse eyes thoroughly with water.

Stop use and ask a doctor if irritation or rash occurs. These may be signs of a serious condition.

Keep out of reach of children. If swallowed, get medical help or contact a Poison Control Center right away.

Directions

- Place enough product on hands to cover all surfaces. Rub hands together until dry.
- Supervise children under 6 years of age when using this product to avoid swallowing.

Other information

- Store between 15-30C (59-86F)

Inactive ingredients

WATER, GLYCERIN, PROPYLENE GLYCOL, AMINOMETHYLPROPANOL, PHENOXYETHANOL / IODOPROPYNLBUTYLCARBAMATE, TETRASODIUM EDTA, EXT. VIOLET 2

Package Label - Principal Display Panel

3785 mL NDC: 75470-800-01

960 mL NDC: 75470-800-02

500 mL NDC: 75470-800-01

490 mL NDC: 75470-800-04